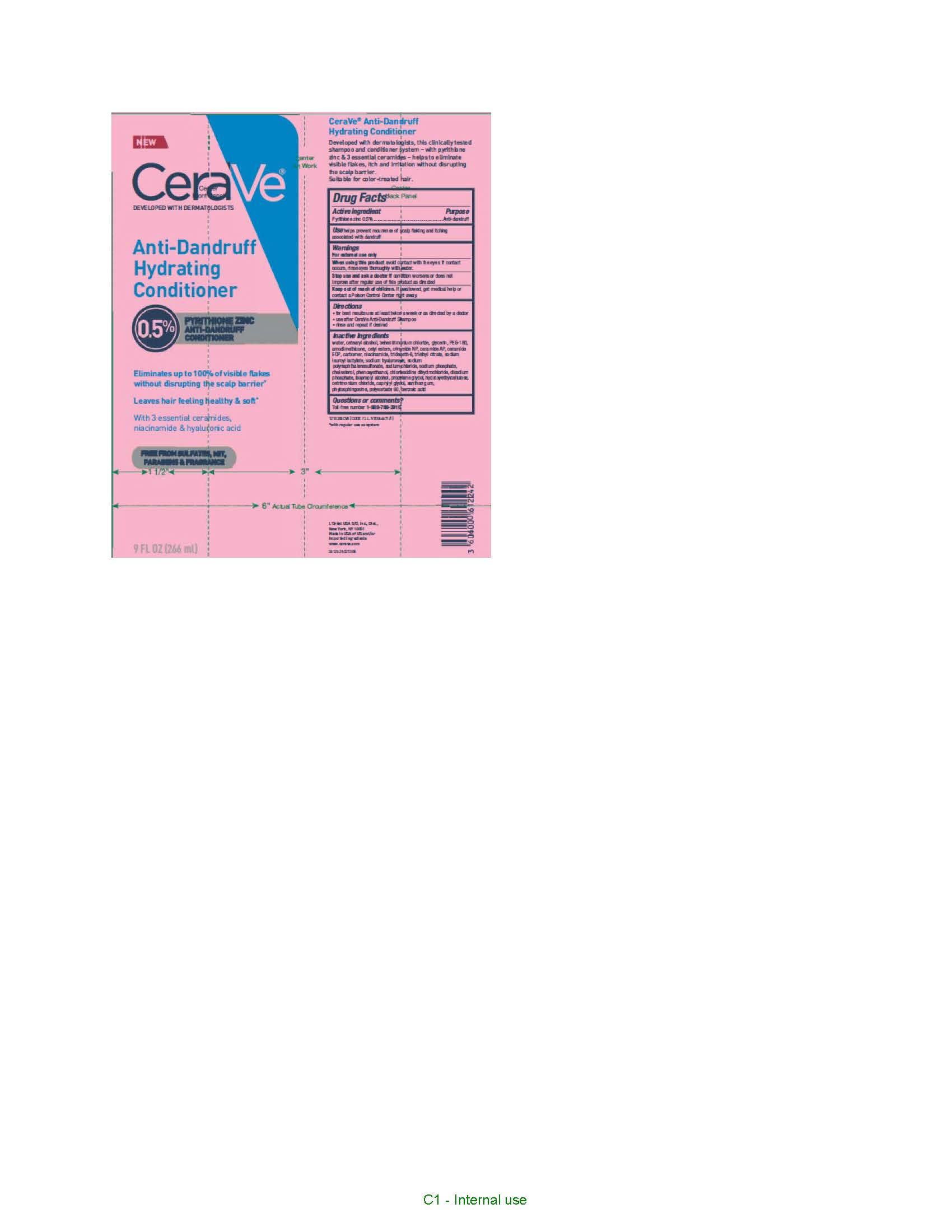 DRUG LABEL: CeraVe Anti-Dandruff Hydrating Conditioner
NDC: 49967-242 | Form: LIQUID
Manufacturer: L'Oreal USA Products Inc
Category: otc | Type: HUMAN OTC DRUG LABEL
Date: 20241217

ACTIVE INGREDIENTS: PYRITHIONE ZINC 5 mg/1 mL
INACTIVE INGREDIENTS: WATER; CETEARYL ALCOHOL; BEHENTRIMONIUM CHLORIDE; GLYCERIN; PEG-180; AMODIMETHICONE (1300 CST); CETYL ESTERS; CERAMIDE NP; CERAMIDE AP; CARBOMER; NIACINAMIDE; TRIDECETH-6; TRIETHYL CITRATE; SODIUM LAUROYL LACTYLATE; SODIUM HYALURONATE; SODIUM CHLORIDE; SODIUM PHOSPHATE; CHOLESTEROL; PHENOXYETHANOL; CHLORHEXIDINE DIHYDROCHLORIDE; DISODIUM PHOSPHATE; ISOPROPYL ALCOHOL; PROPYLENE GLYCOL; HYDROXYETHYLCELLULOSE; CETRIMONIUM CHLORIDE; CAPRYLYL GLYCOL; XANTHAN GUM; PHYTOSPHINGOSINE; POLYSORBATE 60; BENZOIC ACID

Drug Facts

Active ingredient

Pyrithione zinc 0.5%

Purpose

Anti-dandruff

Use

helps prevents recurrence of scalp flaking and itching associated with dandruff

Warnings

For external use only

When using this product

avoid contact with the eyes. If contact occurs, rinse eyes throughly with water.

Stop use and ask a doctor if

condition worsens or does not improve after regular use of this product as directed

Keep out of reach of children.

If swallowed, get medical help or contact a Poison Control Center right away.

Directions

- for best results use at least twice a week or as directed by a doctor
- use after CeraVe Anti-Dandruff Shampoo
- rinse and repeat if desired

Inactive ingredients

water, cetearyl alcohol, behentrimonium chloride, glycerin, PEG-180, amodimethicone, cetyl esters, ceramide NP, ceramide AP, ceramide EOP, carbomer, niacinamide, trideceth-6, triethyl citrate, sodium lauroyl lactylate, sodium hyaluronate, sodium polynaphthalenesulfonate, sodium chloride, sodium phosphate, cholesterol, phenoxyethanol, chlorhexidine dihydrochloride, disodium phosphate, isopropyl alcohol, propylene glycol, hydroxyethylcellulose, cetrimonium chloride, caprylyl glydol, xanthan gum, phytosphingosine, polysorbate 60, benzoic acid

Questions or comments?

Toll-free number 1-888-768-2915